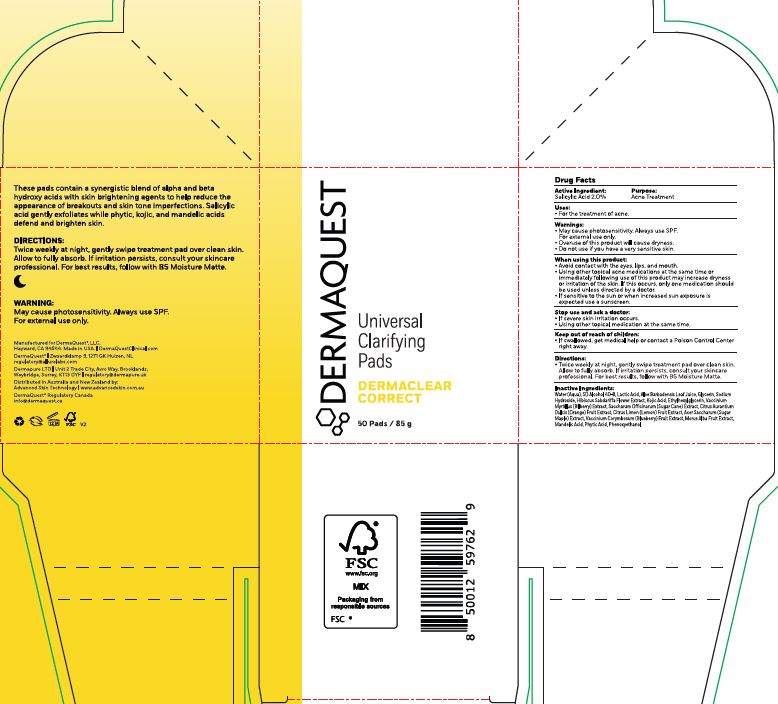 DRUG LABEL: Universal Clarifying Pad
NDC: 62742-4276 | Form: LIQUID
Manufacturer: Allure Labs
Category: otc | Type: HUMAN OTC DRUG LABEL
Date: 20260107

ACTIVE INGREDIENTS: SALICYLIC ACID 20 mg/1 g
INACTIVE INGREDIENTS: LACTIC ACID; KOJIC ACID; SUGARCANE; MANDELIC ACID; ACER SACCHARUM BARK/SAP; WATER; VACCINIUM CORYMBOSUM (BLUEBERRY) FRUIT; BILBERRY; WHITE MULBERRY; LEMON; SODIUM HYDROXIDE; HIBISCUS SABDARIFFA FLOWER; ALCOHOL; GLYCERIN; PHENOXYETHANOL; ALOE BARBADENSIS LEAF JUICE; ORANGE; ETHYLHEXYLGLYCERIN; PHYTIC ACID

Drug Facts

Active Ingredient: Salicylic Acid 2.0%

Purpose:Acne Treatment

Uses:
For the treatment of acne.

Warnings:
• May cause photosensitivity. Always use SPF. For external use only.
• Overuse of this product will cause dryness.
• Do not use if you have a very sensitive skin.

Do not use if you have a very sensitive skin.

When using this product
• Avoid contact with the eyes, lips, and mouth.
• Using other topical acne medications at the same time or immediately following use of this product may increase dryness or irritation of the skin. If this occurs, only one medication should be used unless directed by a doctor.
• If sensitive to the sun or when increased sun exposure is expected use a sunscreen.

Stop use and ask a doctor:
• If severe skin irritation occurs.
• Using other topical medication at the same time.

Keep out of reach of children:
• If swallowed, get medical help or contact a Poison Control Center right away.

Directions:
• Twice weekly at night, gently swipe treatment pad over clean skin. Allow to fully absorb. If irritation persists, consult your skincare professional. For best results, follow with B5 Moisture Matte.

OTHER SAFETY INFORMATION

N/A

Inactive ingredients:
Water (Aqua), SD Alcohol 40-B, Lactic Acid, Aloe Barbadensis Leaf Juice, Glycerin, Sodium Hydroxide, Hibiscus Sabdariffa Flower Extract, Kojic Acid, Ethylhexylglycerin, Vaccinium Myrtillus (Bilberry) Extract, Saccharum Officinarum (Sugar Cane) Extract, Citrus Aurantium Dulcis (Orange) Fruit Extract, Citrus Limon (Lemon) Fruit Extract, Acer Saccharum (Sugar Maple) Extract, Vaccinium Corymbosum (Blueberry) Fruit Extract, Morus Alba Fruit Extract, Mandelic Acid, Phytic Acid, Phenoxyethanol